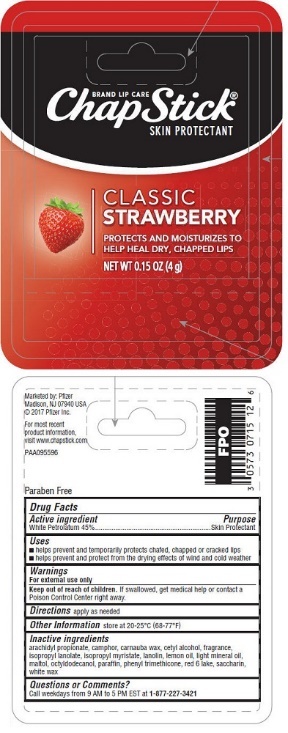 DRUG LABEL: ChapStick Classic Strawberry
NDC: 0573-0715 | Form: STICK
Manufacturer: Haleon US Holdings LLC
Category: otc | Type: HUMAN OTC DRUG LABEL
Date: 20240321

ACTIVE INGREDIENTS: PETROLATUM 450 mg/1 g
INACTIVE INGREDIENTS: ARACHIDYL PROPIONATE; CAMPHOR (NATURAL); CARNAUBA WAX; CETYL ALCOHOL; ISOPROPYL MYRISTATE; LANOLIN; LEMON OIL, COLD PRESSED; LIGHT MINERAL OIL; MALTOL; OCTYLDODECANOL; PARAFFIN; PHENYL TRIMETHICONE; D&C RED NO. 6; SACCHARIN; WHITE WAX

Drug Facts

Active ingredient

White Petrolatum 45%

Purpose

Skin Protectant

Uses

- helps prevent and temporarily protects chafed, chapped or cracked lips
- helps prevent and protect from the drying effects of wind and cold weather

Warnings

For external use only

Keep out of reach of children. If swallowed, get medical help or contact a Poison Control Center right away.

Directions

apply as needed

Other Information

store at 20-25°C (68-77°F)

Inactive ingredients

arachidyl propionate, camphor, carnauba wax, cetyl alcohol, fragrance, isopropyl lanolate, isopropyl myristate, lanolin, lemon oil, light mineral oil, maltol, octyldodecanol, paraffin, phenyl trimethicone, red 6 lake, saccharin, white wax

Questions or Comments?

Call weekdays from 9 AM to 5 PM EST at 1-877-227-3421

Additional information

Marketed by: Pfizer

Madison, NJ 07940 USA

© 2017 Pfizer Inc.

For most recent product information, visit www.chapstick.com

Paraben Free

PRINCIPAL DISPLAY PANEL

BRAND LIP CARE
ChapStick®
SKIN PROTECTANT

CLASSIC
STRAWBERRY

PROTECTS AND MOISTURIZES TO
HELP HEAL DRY, CHAPPED LIPS

NET WT 0.15 OZ (4 g)